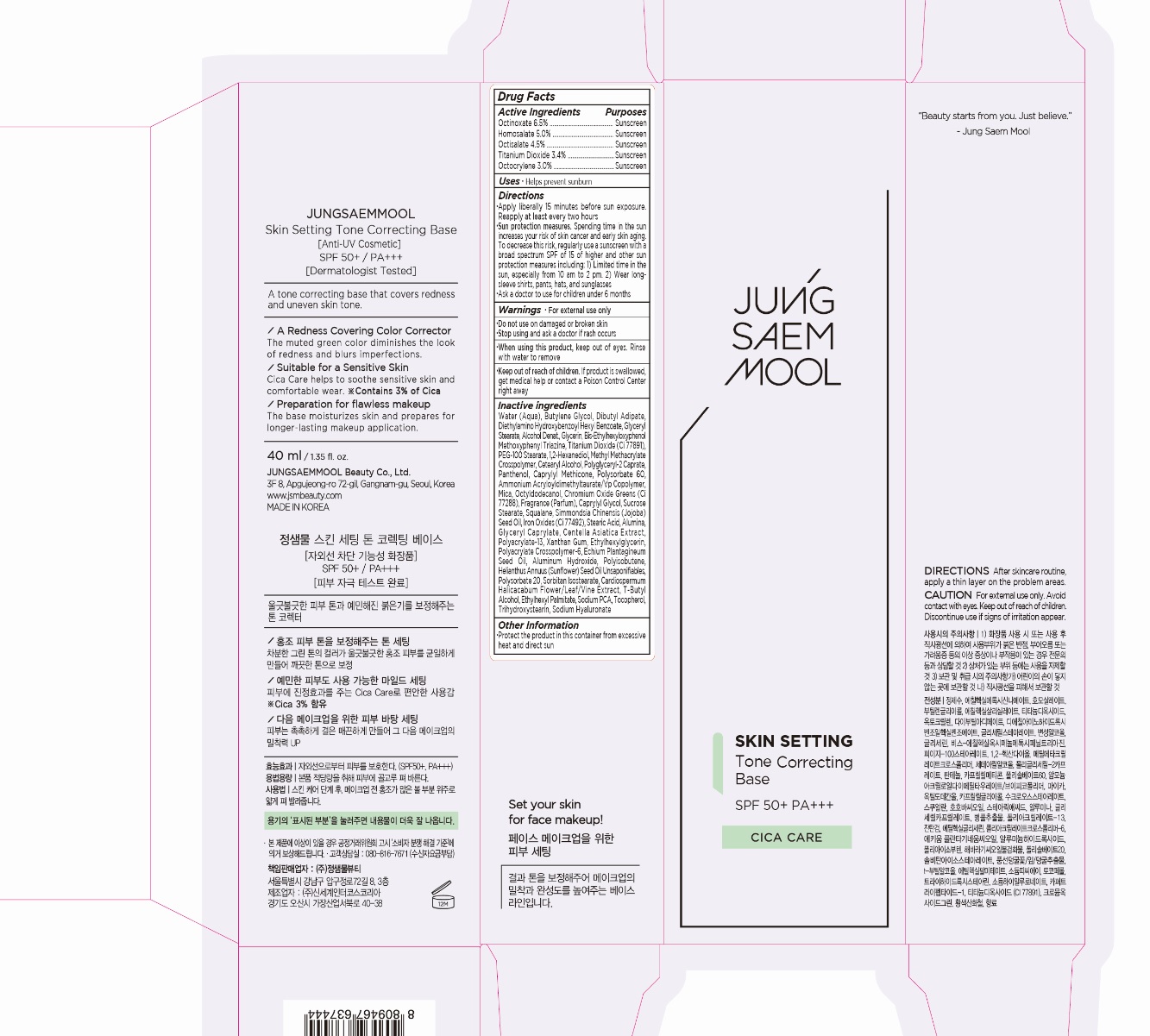 DRUG LABEL: JUNGSAEMMOOL Skin Setting Tone Correcting Base
NDC: 71261-009 | Form: CREAM
Manufacturer: Jungsaemmool Beauty Co., Ltd.
Category: otc | Type: HUMAN OTC DRUG LABEL
Date: 20200714

ACTIVE INGREDIENTS: OCTINOXATE 65 mg/1 mL; HOMOSALATE 50 mg/1 mL; OCTISALATE 45 mg/1 mL; TITANIUM DIOXIDE 34 mg/1 mL; OCTOCRYLENE 30 mg/1 mL
INACTIVE INGREDIENTS: WATER; BUTYLENE GLYCOL; DIBUTYL ADIPATE; DIETHYLAMINO HYDROXYBENZOYL HEXYL BENZOATE; GLYCERYL MONOSTEARATE; GLYCERIN; BEMOTRIZINOL; PEG-100 STEARATE; 1,2-HEXANEDIOL; METHYL METHACRYLATE/GLYCOL DIMETHACRYLATE CROSSPOLYMER; CETOSTEARYL ALCOHOL; POLYGLYCERYL-2 CAPRATE; PANTHENOL; CAPRYLYL TRISILOXANE; POLYSORBATE 60; AMMONIUM ACRYLOYLDIMETHYLTAURATE/VP COPOLYMER; MICA; OCTYLDODECANOL; CHROMIC OXIDE; CAPRYLYL GLYCOL; SUCROSE STEARATE; SQUALANE; JOJOBA OIL; FERRIC OXIDE YELLOW; STEARIC ACID; ALUMINUM OXIDE; GLYCERYL MONOCAPRYLATE; CENTELLA ASIATICA WHOLE; XANTHAN GUM; ETHYLHEXYLGLYCERIN; AMMONIUM ACRYLOYLDIMETHYLTAURATE, DIMETHYLACRYLAMIDE, LAURYL METHACRYLATE AND LAURETH-4 METHACRYLATE COPOLYMER, TRIMETHYLOLPROPANE TRIACRYLATE CROSSLINKED (45000 MPA.S); ECHIUM PLANTAGINEUM SEED OIL; ALUMINUM HYDROXIDE; POLYISOBUTYLENE (1000 MW); POLYSORBATE 20; SORBITAN ISOSTEARATE; TERT-BUTYL ALCOHOL; ETHYLHEXYL PALMITATE; SODIUM PYRROLIDONE CARBOXYLATE; TOCOPHEROL; TRIHYDROXYSTEARIN; HYALURONATE SODIUM; PREZATIDE COPPER

71261-009_JUNGSAEMMOOL Skin Setting Tone Correcting Base

ACTIVE INGREDIENT

Octinoxate 6.5%
Homosalate 5.0%
Octisalate 4.5%
Titanium Dioxide 3.4%
Octocrylene 3.0%

PURPOSE

Sunscreen

INDICATIONS AND USAGE

Helps prevent sunburn

DOSAGE AND ADMINISTRATION

Apply liberally 15 minutes before sun exposure. Reapply at least every two hours

Sun protection measures. Spending time in the sun increases your risk of skin cancer and early skin aging. To decrease this risk, regularly use a sunscreen with a broad spectrum SPF of 15 of higher and other sun protection measures including: 1) Limited time in the sun, especially from 10 am to 2 pm. 2) Wear long-sleeve shirts, pants, hats, and sunglasses

Ask a doctor to use for children under 6 months

WARNINGS

For external use only

Do not use on damaged or broken skin

When using this product, keep out of eyes. Rinse with water to remove.

Stop using and ask a doctor if rash occurs.

KEEP OUT OF REACH OF CHILDREN

Keep out of reach of the children. If product is swallowed, get medical help or contact a poison control center right away.

INACTIVE INGREDIENT

WATER (AQUA), BUTYLENE GLYCOL, DIBUTYL ADIPATE, DIETHYLAMINO HYDROXYBENZOYL HEXYL BENZOATE, GLYCERYL STEARATE, ALCOHOL DENAT., GLYCERIN, BIS-ETHYLHEXYLOXYPHENOL METHOXYPHENYL TRIAZINE, TITANIUM DIOXIDE (CI 77891), PEG-100 STEARATE, 1,2-HEXANEDIOL, METHYL METHACRYLATE CROSSPOLYMER, CETEARYL ALCOHOL, POLYGLYCERYL-2 CAPRATE, PANTHENOL, CAPRYLYL METHICONE, POLYSORBATE 60, AMMONIUM ACRYLOYLDIMETHYLTAURATE/VP COPOLYMER, MICA, OCTYLDODECANOL, CHROMIUM OXIDE GREENS (CI 77288), FRAGRANCE (PARFUM), CAPRYLYL GLYCOL, SUCROSE STEARATE, SQUALANE, SIMMONDSIA CHINENSIS (JOJOBA) SEED OIL, IRON OXIDES (CI 77492), STEARIC ACID, ALUMINA, GLYCERYL CAPRYLATE, CENTELLA ASIATICA EXTRACT, POLYACRYLATE-13, XANTHAN GUM, ETHYLHEXYLGLYCERIN, POLYACRYLATE CROSSPOLYMER-6, ECHIUM PLANTAGINEUM SEED OIL, ALUMINUM HYDROXIDE, POLYISOBUTENE, HELIANTHUS ANNUUS (SUNFLOWER) SEED OIL UNSAPONIFIABLES, POLYSORBATE 20, SORBITAN ISOSTEARATE, CARDIOSPERMUM HALICACABUM FLOWER/LEAF/VINE EXTRACT, t-BUTYL ALCOHOL, ETHYLHEXYL PALMITATE, SODIUM PCA, TOCOPHEROL, TRIHYDROXYSTEARIN, SODIUM HYALURONATE, COPPER TRIPEPTIDE-1

OTHER SAFETY INFORMATION

Protect the product in the container from excessive heat and direct sun